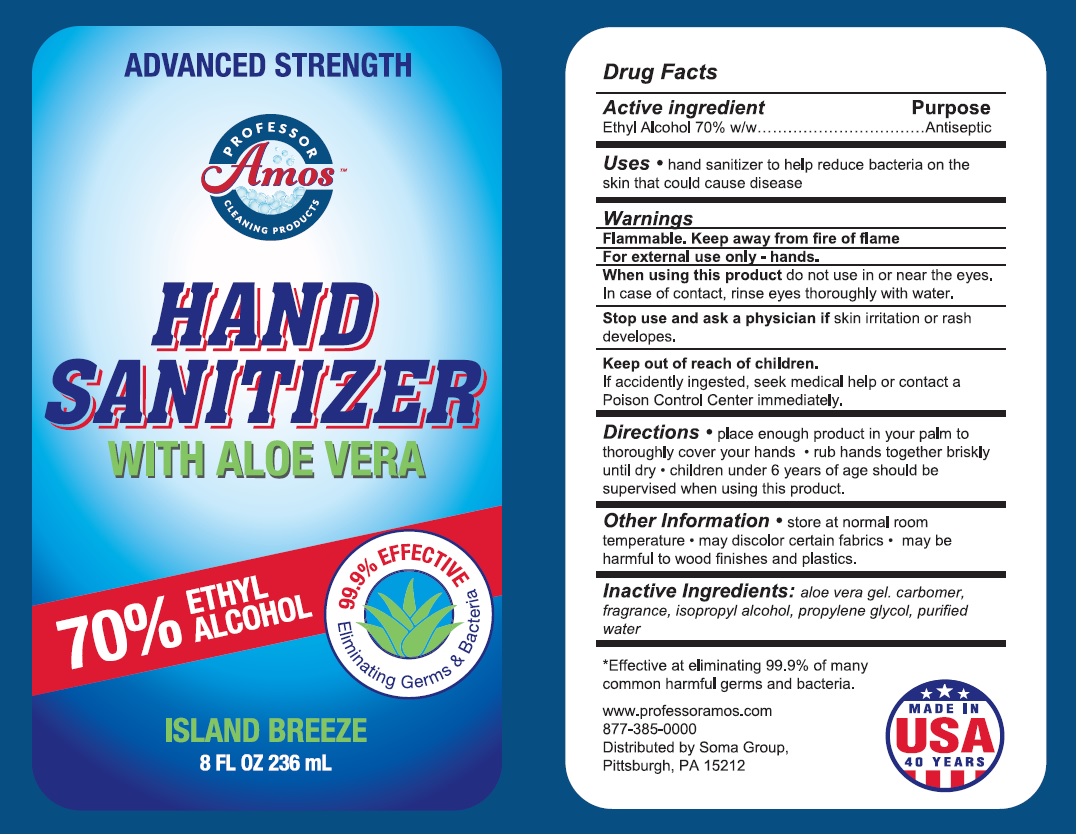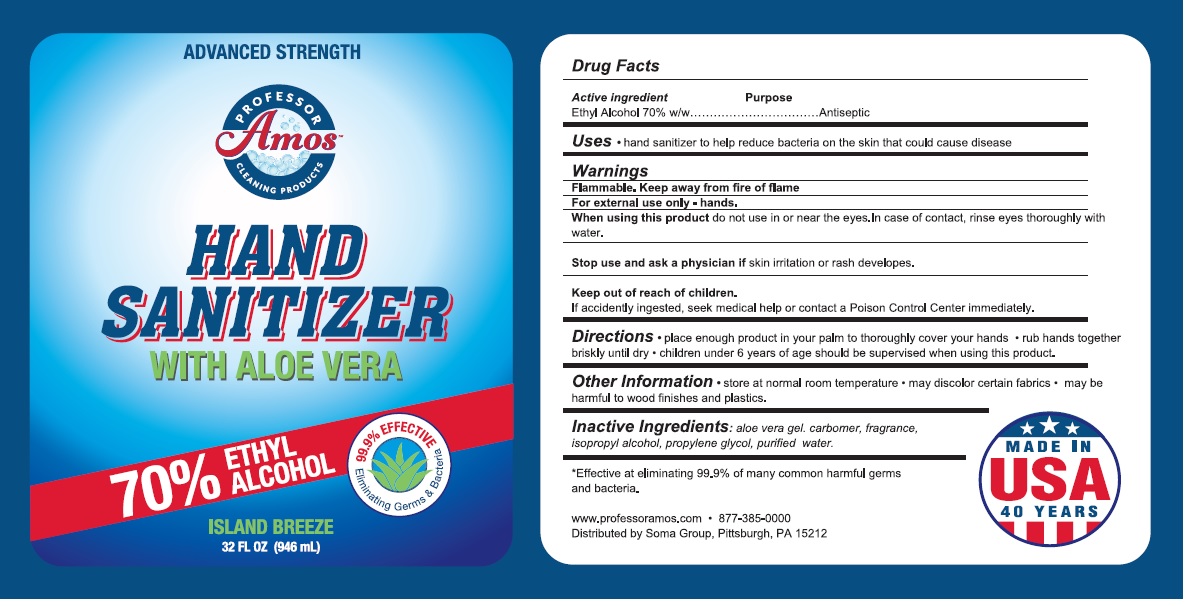 DRUG LABEL: PROFESSOR AMOS HAND SANITIZER
NDC: 80009-664 | Form: GEL
Manufacturer: Soma Group Llc
Category: otc | Type: HUMAN OTC DRUG LABEL
Date: 20220204

ACTIVE INGREDIENTS: ALCOHOL 70 mL/100 mL
INACTIVE INGREDIENTS: ALOE VERA LEAF; CARBOMER HOMOPOLYMER, UNSPECIFIED TYPE; ISOPROPYL ALCOHOL; PROPYLENE GLYCOL; WATER

PROFESSOR Amos™ CLEANING PRODUCTS HAND SANITIZER

Active ingredient

Ethyl Alcohol 70% w/w

Purpose

Antiseptic

Uses

• hand sanitizer to help reduce bacteria on the skin that could cause disease

Warnings

Flammable. Keep away from fire or flame

For external use only - hands.

When using this product do not use in or near the eyes. In case of contact, rinse eyes thoroughly with water.

Stop use and ask a physician if skin irritation or rash develops.

Keep out of reach of children.

If accidently ingested, seek medical help or contact a Poison Control Center immediately.

Directions

• place enough product in your palm to thoroughly cover your hands • rub hands together briskly until dry • children under 6 years of age should be supervised when using this product.

Other Information

• store at normal room temperature • may discolor certain fabrics • may be harmful to wood finishes and plastics.

Inactive Ingredients:

aloe vera gel, carbomer, fragrance, isopropyl alcohol, propylene glycol, purified water

ADVANCED STRENGTH

HAND SANITIZER WITH ALOE VERA

70% ETHYL ALCOHOL

99.9% EFFECTIVE

Eliminating Germs & Bacteria

ISLAND BREEZE

*Effective at eliminating 99.9% of many common harmful germs and bacteria.

www.professoramos.com

877-385-0000

Distributed by Soma Group,

Pittsburgh, PA 15212

MADE IN USA 40 YEARS